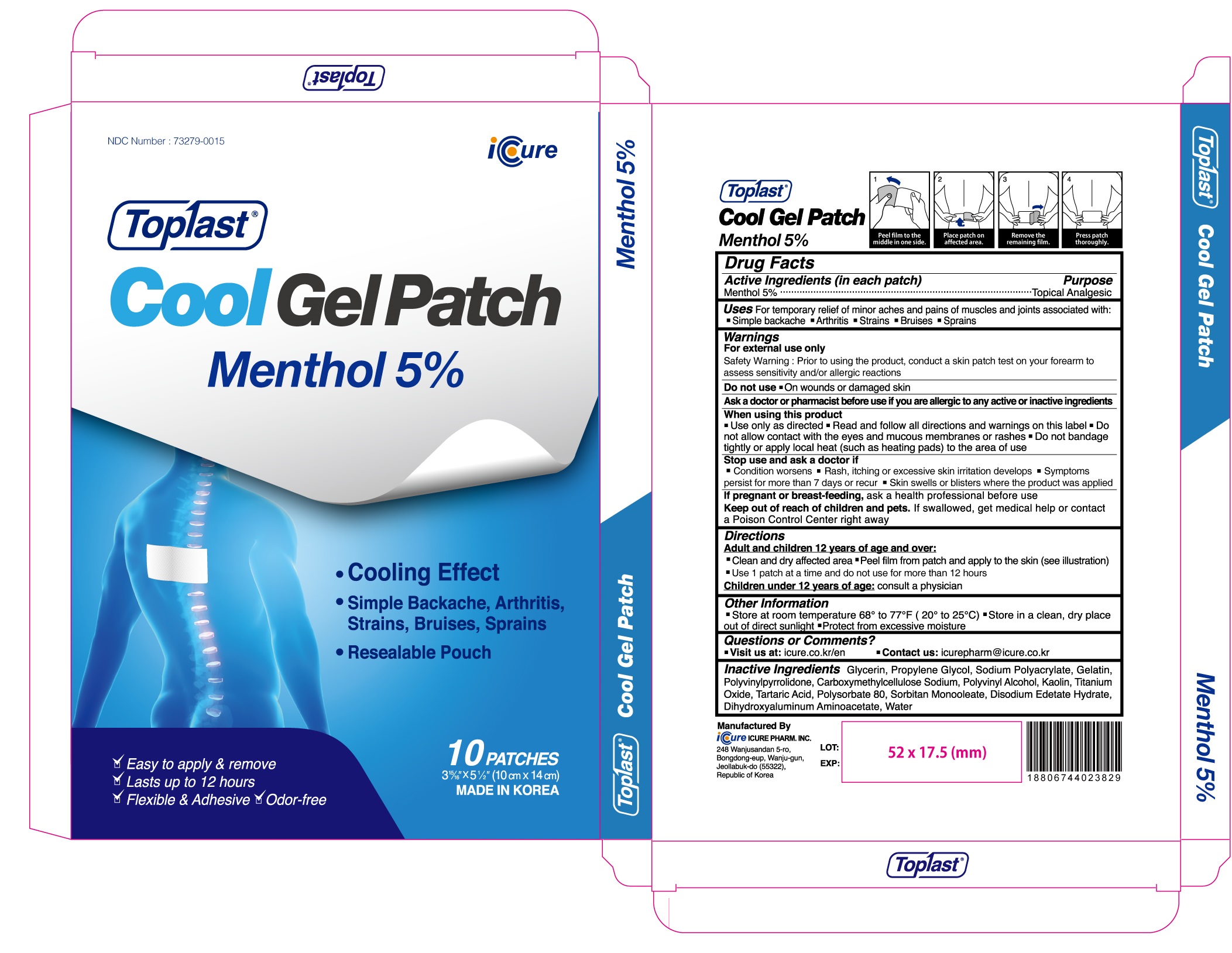 DRUG LABEL: Toplast Cool Menthol 5percent
NDC: 73279-0015 | Form: PATCH
Manufacturer: Icure Pharmaceutical Inc, Wanju Factory
Category: otc | Type: HUMAN OTC DRUG LABEL
Date: 20210423

ACTIVE INGREDIENTS: Menthol 375 mg/1 1
INACTIVE INGREDIENTS: Glycerin; Propylene Glycol; Gelatin; CARBOXYMETHYLCELLULOSE SODIUM, UNSPECIFIED; Kaolin; TITANIUM DIOXIDE; Tartaric Acid; Polysorbate 80; SORBITAN MONOOLEATE; EDETATE DISODIUM; Dihydroxyaluminum Aminoacetate; Water

Drug Facts

Active Ingredients (in each patch)

Menthol 5%

INACTIVE INGREDIENTS

Glycerin, Propylene Glycol, Sodium Polyacrylate, Gelatin, Polyvinylpyrrolidone, Carboxymethylcellulose Sodium, Polyvinyl Alcohol, Kaolin, Titanium Oxide, Tartaric Acid, Polysorbate 80, Sorbitan Monooleate, Disodium Edetate Hydrate, Dihydroxyaluminum Aminoacetate, Water

PURPOSE

Topical Analgesic

WARNINGS

For external use only
Safety Warning : Prior to using the product, conduct a skin patch test on your forearm to assess sensitivity and/or allergic reactions
--------------------------------------------------------------------------------------------------------
Do not use
■ On wounds or damaged skin
--------------------------------------------------------------------------------------------------------
Ask a doctor or pharmacist before use if you are allergic to any active or inactive ingredients
--------------------------------------------------------------------------------------------------------
When using this product
■ Use only as directed ■ Read and follow all directions and warnings on this label ■ Do not allow contact with the eyes and mucous membranes or rashes ■ Do not bandage tightly or apply local heat (such as heating pads) to the area of use
--------------------------------------------------------------------------------------------------------
Stop use and ask a doctor if
■ Condition worsens ■ Rash, itching or excessive skin irritation develops ■ Symptoms persist for more than 7 days or recur ■ Skin swells or blisters where the product was applied
--------------------------------------------------------------------------------------------------------
If pregnant or breast-feeding, ask a health professional before use
Keep out of reach of children and pets. If swallowed, get medical help or contact a Poison Control Center right away

Keep out of reach of children and pets

If swallowed, get medical help or contact a Poison Control Center right away

Uses

For temporary relief of minor aches and pains of muscles and joints associated with : ■ Simple backache ■ Arthritis ■ Strains ■ Bruises ■ Sprains

Directions

Adult and children 12 years of age and over :
■ Clean and dry affected area ■ Peel film from patch and apply to the skin (see illustration) ■ Use 1 patch at a time and do not use for more than 12 hours
Children under 12 years of age : consult a physician

Other Information

■ Store at room temperature 68° to 77°F (20° to 25°C) ■ Store in a clean, dry place out of direct sunlight ■ Protect from excessive moisture

Questions or Comments

■ Visit us at : icure.co.kr/en ■ Contact us : icurepharm@icure.co.kr